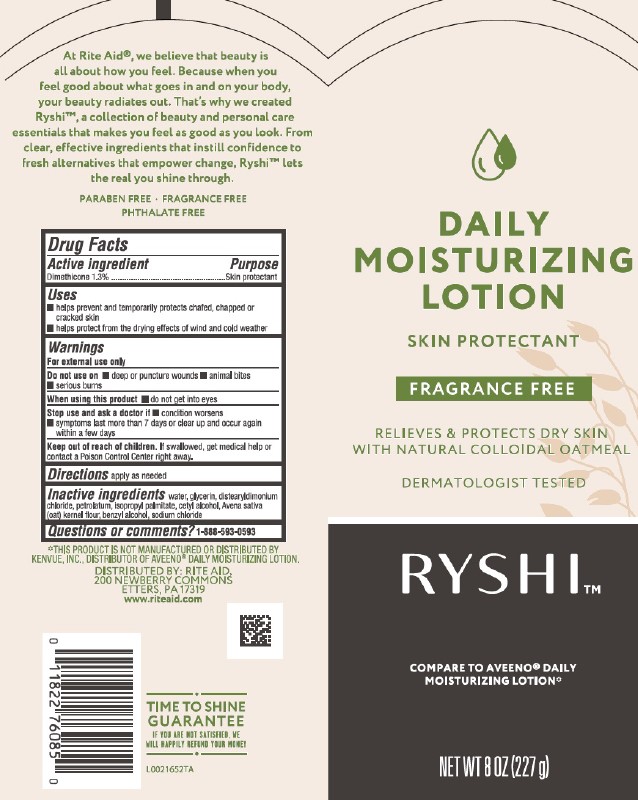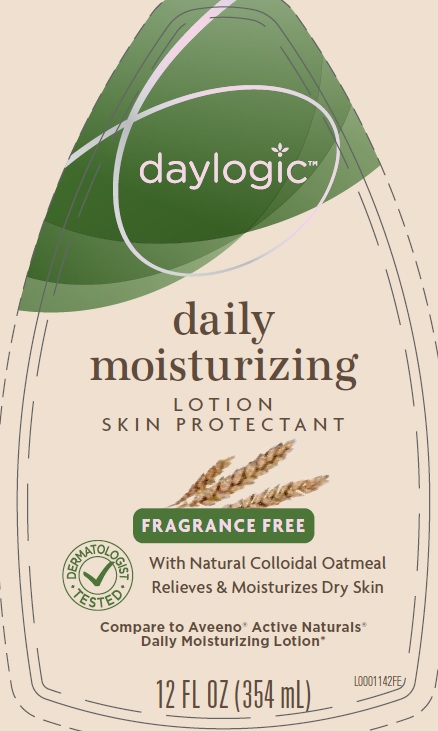 DRUG LABEL: Daily Moisturizing
NDC: 11822-0619 | Form: LOTION
Manufacturer: Rite Aid Corporation
Category: otc | Type: HUMAN OTC DRUG LABEL
Date: 20260130

ACTIVE INGREDIENTS: DIMETHICONE 13 mg/1 mL
INACTIVE INGREDIENTS: WATER; GLYCERIN; DISTEARYLDIMONIUM CHLORIDE; PETROLATUM; ISOPROPYL PALMITATE; CETYL ALCOHOL; OATMEAL; BENZYL ALCOHOL; SODIUM CHLORIDE

Ryshi_Daylogic 619.003/619AC rev2
Daily Moisturizing Lotion

Claims

At Rite Aid, we believe that beauty is all about how you feel. Because when you feel good about what goes in and on your body, your beauty radiates out. That's why we created Ryshi, a collection of beauty and personal care essentials that makes you feel as good as you look. From clear, effective ingredients that instill confidence to fresh alternatives that empower change, Ryshi lets the real you shine through.

PARABEN FREE

FRAGRANCE FREE

PHTHALATE FREE

active ingredient

Dimethicone 1.3%

Purpose

Skin protectant

Uses

- helps prevent and temporarily protects chafed, chapped or cracked skin
- helps protect from the drying effects of wind and cold weather

Warnings

For external use only

Do not use on

- deep or puncture wounds
- animal bites
- serious burns

When using this product

- do not get into eyes

Stop use and ask a doctor if

- condition worsens
- symptoms last more than 7 days or clear up and occur again within a few days

Keep out of reach of children.

If swallowed, get medical help or contact a Poison Control Center right away.

Directions

apply as needed

Inactive ingredients

water, glycerin, distearyldimonium chloride, petrolatum, isopropyl palmitate, cetyl alcohol, Avena sativa (oat) kernel flour, benzyl alcohol, sodium chloride

Disclaimer

*This product is not manufactured or distributed by Kenvue, Inc., distributor of Aveeno®Daily Moisturizing Lotion.

Adverse Reaction

DISTRIBUTED BY: RITE AID

200 NEWBERRY COMMNS

ETTERS, PA 17319

www.riteaid.com

TIME TO SHINE GUARANTEE

If you are not satisfied, we will happily refund your money.

Principal display panel

DAILY MOISTURIZING LOTION

SKIN PROTECTANT

FRAGRANCE FREE

RELIEVES & PROTECTS DRY SKIN WITH NATURAL COLLODIAL OATMEAL

DERMATOLOGIST TESTED

RYSHI™

COMPARE TO AVEENO® DAILY MOISTURIZING LOTION*

NET WT 8 OZ (227 g)

Principal display panel

daylogic

daily

moisturizing

LOTION

SKIN PROTECTANT

FRAGRANCE FREE

DERATOLOGIST TESTED

With Natural Collodal Oatmeal

Relieves & Moisturizing Lotion

Compare to Aveeno Active Natural

Daily Moisturizing Lotion

12 FL OZ (354 mL)